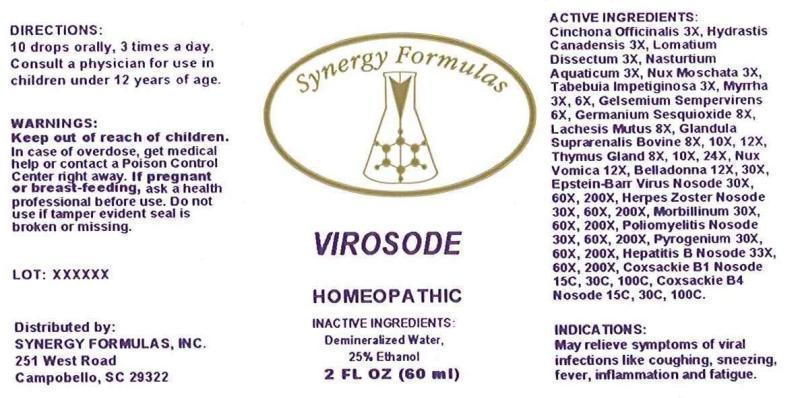 DRUG LABEL: Virosode
NDC: 43772-0046 | Form: LIQUID
Manufacturer: Synergy Formulas, Inc
Category: homeopathic | Type: HUMAN OTC DRUG LABEL
Date: 20150311

ACTIVE INGREDIENTS: CINCHONA OFFICINALIS BARK 3 [hp_X]/1 mL; GOLDENSEAL 3 [hp_X]/1 mL; LOMATIUM DISSECTUM ROOT 3 [hp_X]/1 mL; NASTURTIUM OFFICINALE 3 [hp_X]/1 mL; NUTMEG 3 [hp_X]/1 mL; TABEBUIA IMPETIGINOSA BARK 3 [hp_X]/1 mL; MYRRH 3 [hp_X]/1 mL; GELSEMIUM SEMPERVIRENS ROOT 6 [hp_X]/1 mL; GERMANIUM SESQUIOXIDE 8 [hp_X]/1 mL; LACHESIS MUTA VENOM 8 [hp_X]/1 mL; BOS TAURUS ADRENAL GLAND 8 [hp_X]/1 mL; SUS SCROFA THYMUS 8 [hp_X]/1 mL; STRYCHNOS NUX-VOMICA SEED 12 [hp_X]/1 mL; ATROPA BELLADONNA WHOLE 12 [hp_X]/1 mL; HUMAN HERPESVIRUS 4 30 [hp_X]/1 mL; HUMAN HERPESVIRUS 3 30 [hp_X]/1 mL; MEASLES VIRUS 30 [hp_X]/1 mL; POLIOVIRUS 30 [hp_X]/1 mL; RANCID BEEF 30 [hp_X]/1 mL; HEPATITIS B VIRUS 33 [hp_X]/1 mL; HUMAN COXSACKIEVIRUS B1 15 [hp_C]/1 mL; HUMAN COXSACKIEVIRUS B4 15 [hp_C]/1 mL
INACTIVE INGREDIENTS: WATER; ALCOHOL

DRUG FACTS:

ACTIVE INGREDIENTS:

Cinchona Officinalis 3X, Hydrastis Canadensis 3X, Lomatium Dissectum 3X, Nasturtium Aquaticum 3X, Nux Moschata 3X, Tabebuia Impetiginosa 3X, Myrrha 3X, 6X, Gelsemium Sempervirens 6X, Germanium Sesquioxide 8X, Lachesis Mutus 8X, Glandula Suprarenalis Bovine 8X, 10X, 12X, Thymus Gland (Suis) 8X, 10X, 24X, Nux Vomica 12X, Belladonna 12X, 30X, Epstein-Barr Virus Nosode 30X, 60X, 200X, Herpes Zoster Nosode 30X, 60X, 200X, Morbillinum 30X, 60X, 200X, Poliomyelitis Nosode 30X, 60X, 200X, Pyrogenium 30X, 60X, 200X, Hepatitis B Nosode 33X, 60X, 200X, Coxsackie B1 Nosode 15C, 30C, 100C, Coxsackie B4 Nosode 15C, 30C, 100C

INDICATIONS:

May relieve symptoms of viral infection like coughing, sneezing, fever, inflammation and fatigue.

WARNINGS:

Keep out of reach of children. In case of overdose, get medical help or contact a Poison Control Center right away.

If pregnant or breast-feeding, ask a health professional before use.

Do not use if tamper evident seal is broken or missing.

Keep out of reach of children. In case of overdose, get medical help or contact a Poison Control Center right away.

DIRECTIONS:

10 drops orally, 3 times a day. Consult a physician for use in children under 12 years of age.

INDICATIONS:

May relieve symptoms of viral infection like coughing, sneezing, fever, inflammation and fatigue.

INACTIVE INGREDIENTS:

Demineralized Water, 25% Ethanol

QUESTIONS:

Distributed by:

SYNERGY FORMULAS, INC.

251 West Road

Campobello, SC 29322

PACKAGE LABEL DISPLAY:

Synergy Formulas

VIROSODE

HOMEOPATHIC

2 FL OZ (60 ml)